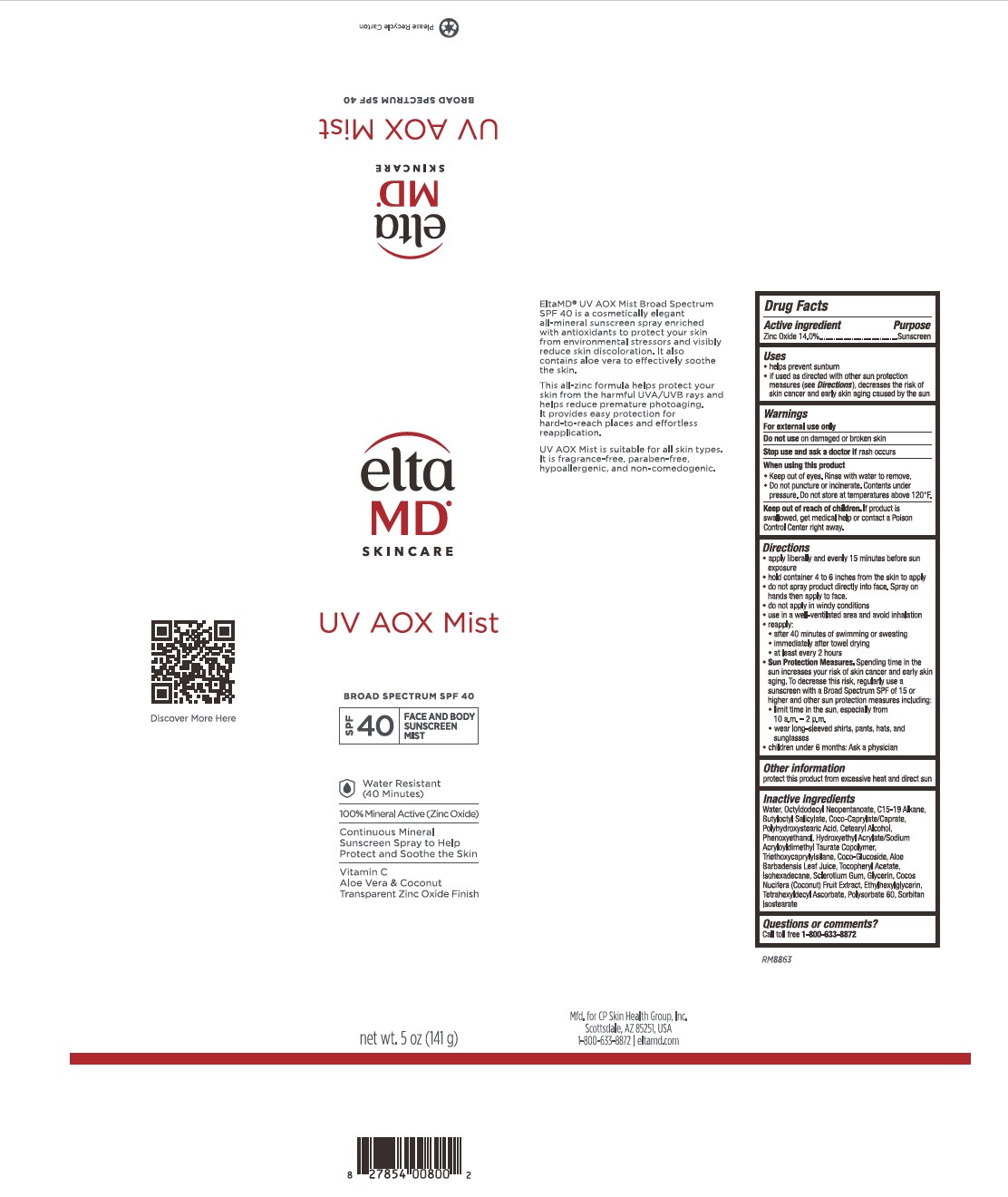 DRUG LABEL: EltaMD UV AOX Mist
NDC: 72043-2671 | Form: SPRAY
Manufacturer: CP Skin Health Group, Inc
Category: otc | Type: HUMAN OTC DRUG LABEL
Date: 20231109

ACTIVE INGREDIENTS: ZINC OXIDE 14.0 g/1000 g
INACTIVE INGREDIENTS: WATER; PHENOXYETHANOL; ETHYLHEXYLGLYCERIN; GLYCERIN; COCOS NUCIFERA WHOLE; TRIETHOXYCAPRYLYLSILANE; TETRAHEXYLDECYL ASCORBATE; OCTYLDODECYL NEOPENTANOATE; COCO-CAPRYLATE/CAPRATE; BUTYLOCTYL SALICYLATE; POLYHYDROXYSTEARIC ACID (2300 MW); HYDROXYETHYL ACRYLATE/SODIUM ACRYLOYLDIMETHYL TAURATE COPOLYMER (45000 MPA.S AT 1%); ISOHEXADECANE; POLYSORBATE 60; ALOE VERA LEAF; .ALPHA.-TOCOPHEROL ACETATE, DL-; C15-19 ALKANE; CETOSTEARYL ALCOHOL; COCO GLUCOSIDE; BETASIZOFIRAN

EltaMD UV AOX Mist

Warnings

For external use only

Do not use on damaged or broken skin

Stop use and ask a doctor if rash occurs

When using this product: keep out of eyes, rinse with water to remove. Do not puncture or incinerate. Contents under pressure. Do not store at temperatures above 120F

Active Ingredient

Zinc Oxide 14.0% Sunscreen

Uses

Helps prevent sunburn

If used as directed with other sun protection measures (See Directions), decreases the risk of skin cancer and early skin aging caused by the sun.

Uses

Helps prevent sunburn

If used as directed with other sun protection measures (See Directions), decreases the risk of skin cancer and early skin aging caused by the sun.

Directions

Apply liberally 15 minutes before sun exposure. Hold container 4-6 inches from the skin to apply. Do not spray product directly into face, spray on hands then apply to face. do not apply in windy conditions. Use in a well-ventilated area and avoide inhallation. Reapply after 40 mintues of swimming or sweating, immediately after towel drying and at least every 2 hours. Sun Protection Measures: Spending time in the sun increases your risk of skin cancer and early skin aging. To decrease this risk, regularly use a sunscreen with a broad-spectrum SPF of 15 or higher and other sun protection measures including: limit time in the sun, especially from 10 am to 2 pm. Wear long-sleeve shirts, pants, hats, and sunglasses. Children under 6 months: ask a physician.

Inactive Ingredients

water, octyldodecyl neopentanoate, C15-19 alkane, butyloctyl salicylate, coco-caprylate/caprate, polyhydroxystearic acid, cetearyl alcohol, phenoxyethanol, hydroxyethyl acrylate/sodium acryloyldimethyl taurate copolymer, triethoxycaprylylsilane, coco-glucoside, aloe barbadensis leaf juice, tocopheryl acetate, isohexadecane, scloerolium gum, glycerin, cocos nucifer (coconut) fruit extract, ethylhexylglycerin, tetrahexyldecyl ascorbate, polysorbate 60, sorbitan isostearate

Keep out of reach of children

Questions

Questions or Comments?

Call toll free 1-800-633-8872

Other Information

protect this product from excessive heat and direct sun